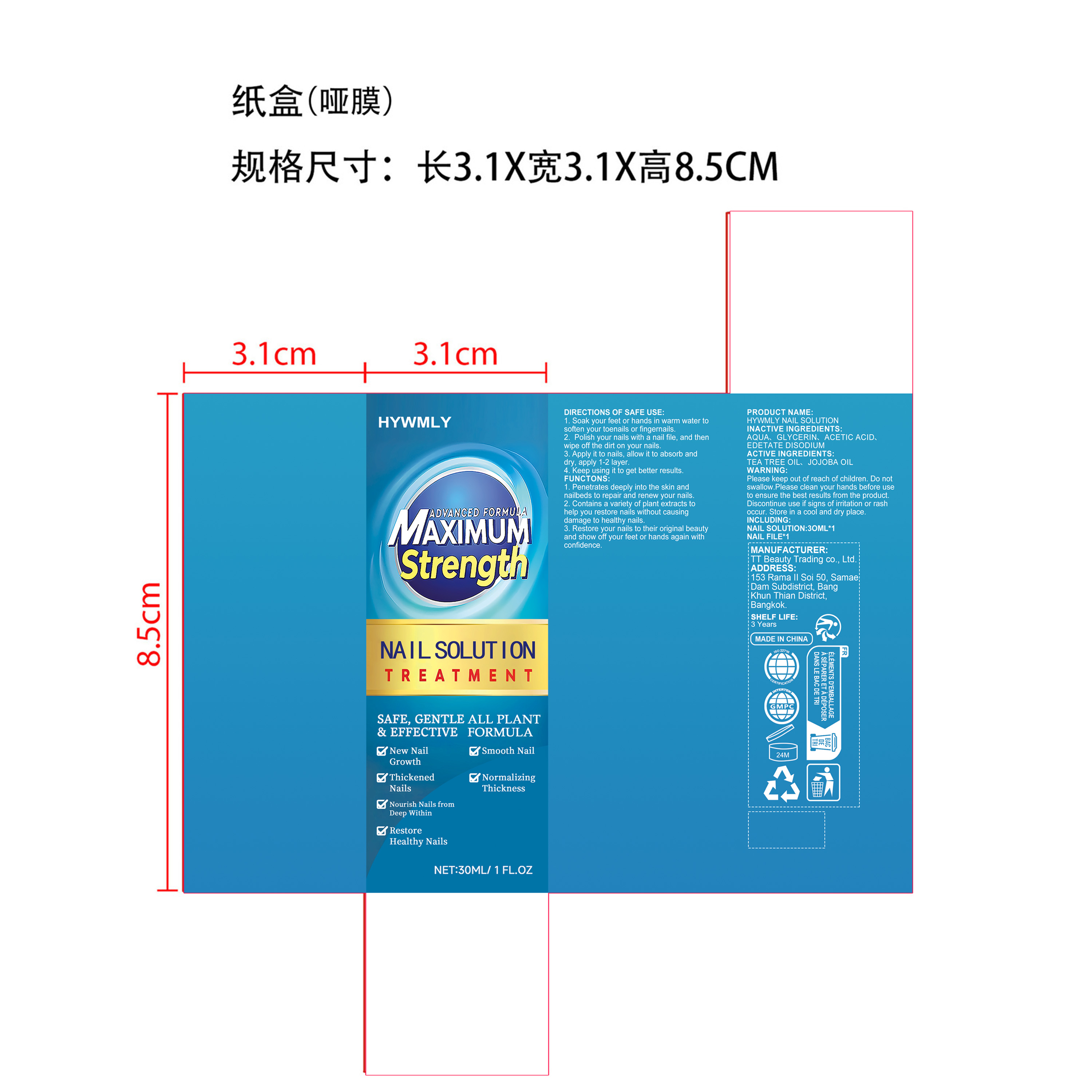 DRUG LABEL: HYWMLY NAIL RENEWAL
NDC: 85206-007 | Form: LIQUID
Manufacturer: TT Beauty Trading Co., Ltd.
Category: otc | Type: HUMAN OTC DRUG LABEL
Date: 20251008

ACTIVE INGREDIENTS: JOJOBA OIL 0.9 mg/30 mg; TEA TREE OIL 0.15 mg/30 mg
INACTIVE INGREDIENTS: EDETATE DISODIUM 0.03 mg/30 mg; GLYCERIN 1.5 mg/30 mg; AQUA 27.12 mg/30 mg; ACETIC ACID 0.3 mg/30 mg

ACTIVE INGREDIENT

TEA TREE OIL、
JOJOBA OIL

INACTIVE INGREDIENT

AQUA、
GLYCERIN、
ACETIC ACID、
EDETATE DISODIUM

WHEN USING

1. Soak your feet or hands in warm water to soften your toenails or fingernails.

2. Polish your nails with a nail file, and then wipe off the dirt on your nails.

3. Apply it to nails, allow it to absorb and dry, apply 1-2 layer.

4. Keep using it to get better results.

PURPOSE

1. Penetrates deeply into the skin and nailbeds to repair and renew your nails.

2. Contains a variety of plant extracts to help you restore nails without causing damage to healthy nails.

3. Restore your nails to their original beauty and show off your feet or hands again with confidence.

WARNINGS

Please keep out of reach of children. Do not swallow.Please clean your hands before use to ensure the best results from the product. Discontinue use if signs of irritation or rash occur. Store in a cool and dry place.

DO NOT USE

Discontinue use if signs of irritation or rash occur.

STOP USE

Discontinue use if signs of irritation or rash occur.

STORAGE AND HANDLING

Store in a cool and dry place.

KEEP OUT OF REACH OF CHILDREN

Please keep out of reach of children. Do not swallow.

DOSAGE AND ADMINISTRATION

1. Soak your feet or hands in warm water to soften your toenails or fingernails.

2. Polish your nails with a nail file, and then wipe off the dirt on your nails.

3. Apply it to nails, allow it to absorb and dry, apply 1-2 layer.

4. Keep using it to get better results.